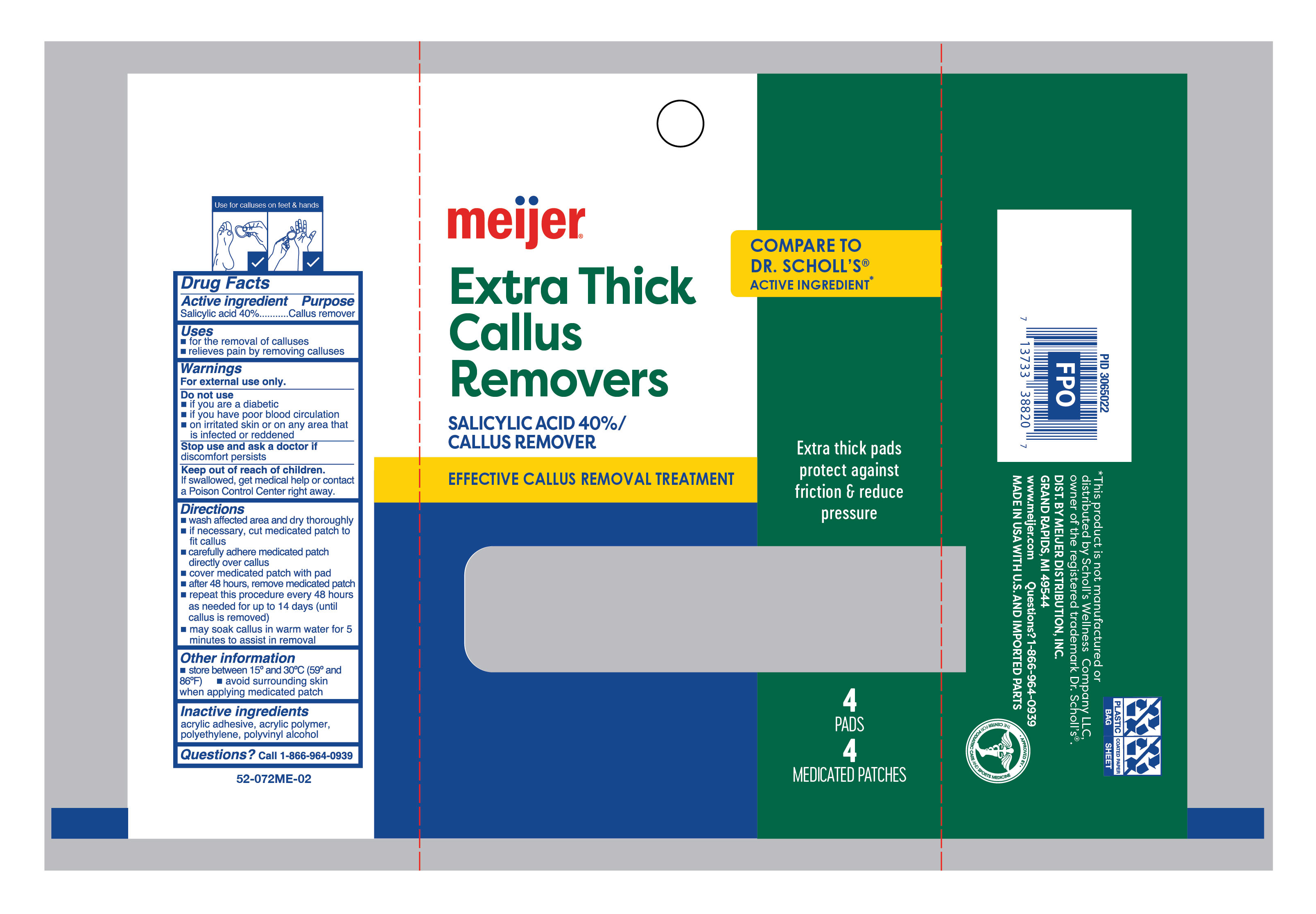 DRUG LABEL: Medicated Callus Removers Extra Thick
NDC: 79481-0611 | Form: PATCH
Manufacturer: Meijer Distribution Inc
Category: otc | Type: HUMAN OTC DRUG LABEL
Date: 20260102

ACTIVE INGREDIENTS: SALICYLIC ACID 400 mg/1 g
INACTIVE INGREDIENTS: POLYVINYL ALCOHOL, UNSPECIFIED; HIGH DENSITY POLYETHYLENE

Meijer Medicated Extra Thick Callus Removers

Active ingredient

Salicylic acid 40%

Purpose

Callus remover

Use

- for the removal of calluses
- relieves pain by removing calluses

Warnings

For external use only.

Do not use

- if you are a diabetic
- if you have poor blood circulation
- on irritated skin, on any area that is infected or reddened

Stop use and ask a doctor

if discomfort persists

Keep out of reach of children.

If swallowed, get medical help or contact a Poison Control Center right away.

Directions

- wash affected area and dry area thoroughly
- if necessary, cut medicated patch to fit callus
- apply adhesive side of medicated patch onto callus
- cover medicated patch with pad
- after 48 hours, remove medicated patch
- repeat procedure every 48 hours as needed for up to 14 days (until callus is removed)
- may soak callus in warm water for 5 minutes to assist in removal

Other information

store between 15° and 30°C (59° and 86°F)

avoid surrounding skin when applying medicated patch

Inactive ingredients

acrylic adhesive, acrylic polymer, polyethylene, polyvinyl alcohol

Questions?

call 1-866-964-0939

Principal Display Panel

meijer

Extra Thick

callus

removers

Salicylic Acid 40%/Callus Remover

Effective callus removal treatment

Extra thick pads protect against friction & reduce pressure

4 Pads | 4 Medicated Patches